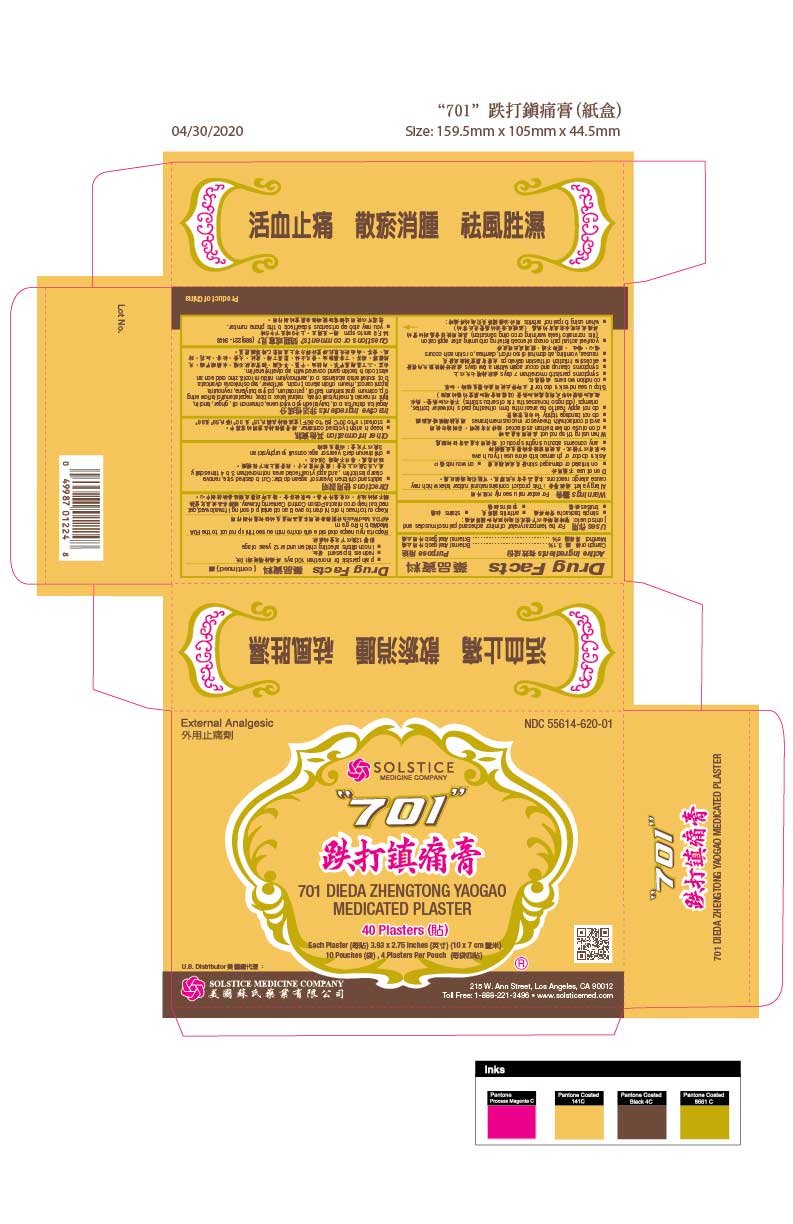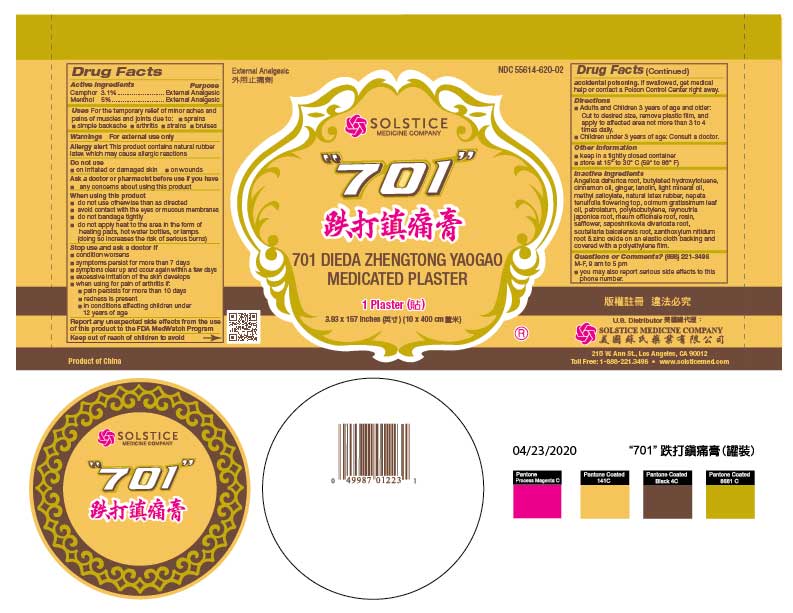 DRUG LABEL: 701 DIEDA ZHENGTONG YAOGAO MEDICATED
NDC: 55614-620 | Form: PLASTER
Manufacturer: MADISON ONE ACME INC
Category: otc | Type: HUMAN OTC DRUG LABEL
Date: 20251110

ACTIVE INGREDIENTS: CAMPHOR (SYNTHETIC) 3.1 g/100 g; MENTHOL 5 g/100 g
INACTIVE INGREDIENTS: ANGELICA DAHURICA ROOT; BUTYLATED HYDROXYTOLUENE; CINNAMON OIL; GINGER; LANOLIN; LIGHT MINERAL OIL; METHYL SALICYLATE; NATURAL LATEX RUBBER; NEPETA TENUIFOLIA FLOWERING TOP; OCIMUM GRATISSIMUM LEAF OIL; PETROLATUM; POLYISOBUTYLENE (800000 MW); REYNOUTRIA JAPONICA ROOT; RHEUM OFFICINALE ROOT; ROSIN; SAFFLOWER; SAPOSHNIKOVIA DIVARICATA ROOT; SCUTELLARIA BAICALENSIS ROOT; ZANTHOXYLUM NITIDUM ROOT; ZINC OXIDE

Drug Facts

Active Ingredients
Camphor 3.1%
Menthol 5%

Purpose
External Analgesic
External Analgesic

Uses
For the temporary relief of minor aches and pains of muscles and joints due to:
■ simple backache ■ arthritis ■ strains ■ bruises ■ sprains

Warnings

For external use only

Allergy alert:This product contains natural rubber latex which may cause allergic reactions.

Do not use
■ on irritated or damaged skin
■ on wounds

Ask a doctor or pharmacist before use if you have
■ any concerns about using this product

When using this product
■ do not use otherwise than as directed
■ avoid contact with the eyes or mucous membranes
■ do not bandage tightly
■ do not apply heat to the area in the form of heating pads, hot water bottles, or lamps (doing so increases the risk of serious burns)

Stop use and ask a doctor if
■ condition worsens
■ symptoms persist for more than 7 days
■ symptoms clear up and occur again within a few days
■ excessive irritation of the skin develops
■ nausea, vomiting, abdominal discomfort, diarrhea, or skin rash occurs
■ you feel actual pain or experience blistering or burning after application (it is normal to feel a warming or cooling sensation)
■ when using for pain of arthritis:
■ pain persists for more than 10 days
■ redness is present
■ in conditions affecting children under 12 years of age

ADVERSE REACTIONS

Report any unexpected side effectsfrom the use of this product to the FDA MedWatch Program

Keep out of reach of children.If swallowed, get medical help or contact a Poison Control Center right away.

Directions
■ Adults and children 3 years of age and older: Cut to desired size, remove clear plastic film, and apply to affected area not more than 3 to 4 times daily.
■ Children under 3 years of age: Consult your physician.

Other information
■ keep in a tightly closed container
■ store at 15º to 30º C (59º to 86º F)

Inactive ingredients
Angelica dahurica root, butylated hydroxytoluene, cinnamon oil, ginger, lanolin, light mineral oil, methyl salicylate, natural latex rubber, nepeta tenuifolia flowering top, ocimum gratissimum leaf oil, petrolatum, polyisobutylene, reynoutria japonica root, rheum officinale root, rosin, safflower, saposhnikovia divaricata root, scutellaria baicalensis root, zanthoxylum nitidum root and zinc oxide on an elastic cloth backing and covered with a polyethylene film.

Questions or comments?
(888) 221-3496 M-F 9 am to 5 pm
■ you may also report serious side effects to this phone number

PACKAGE LABEL

701 DIEDA ZHENGTONG YAOGAO MEDICATED PLASTER

External Analgesic

Camphor and Menthol

NDC 55614-620-02
1 Plaster - 3.93 x 157 inches (10 x 400 cm)

PACKAGE LABEL

701 DIEDA ZHENGTONG YAOGAO MEDICATED PLASTER

External Analgesic

Camphor and Menthol

NDC 55614-620-01

40 Plasters - Each Plaster 3.93 x 2.75 inches (10 x 7 cm)
10 Pouches, 4 Plasters Per Pouch